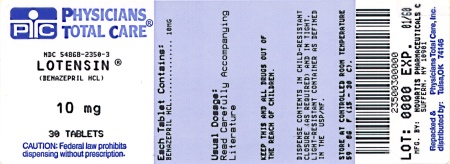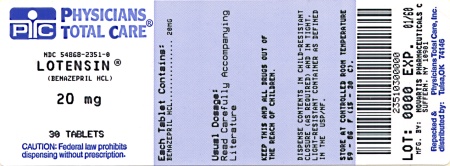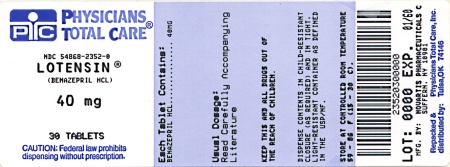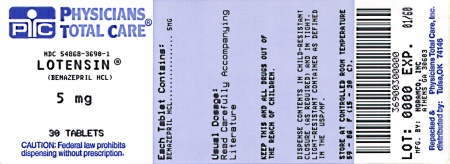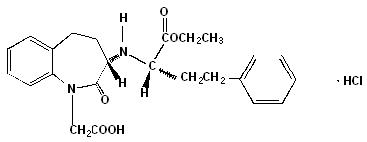 DRUG LABEL: Lotensin
NDC: 54868-3690 | Form: TABLET
Manufacturer: Physicians Total Care, Inc.
Category: prescription | Type: HUMAN PRESCRIPTION DRUG LABEL
Date: 20120301

ACTIVE INGREDIENTS: BENAZEPRIL HYDROCHLORIDE 5 mg/1 1
INACTIVE INGREDIENTS: SILICON DIOXIDE; CROSPOVIDONE; HYDROGENATED CASTOR OIL; HYPROMELLOSES; LACTOSE; CELLULOSE, MICROCRYSTALLINE; POLYSORBATE 80; PROPYLENE GLYCOL; STARCH, POTATO; TALC; TITANIUM DIOXIDE

Lotensin

Lotensin®

(benazepril hydrochloride)

Tablets

Rx only

Prescribing Information

WARNING: FETAL TOXICITY

When pregnancy is detected, discontinue Lotensin as soon as possible.

Drugs that act directly on the renin-angiotensin system can cause injury and death to the developing fetus. See Warnings: Fetal Toxicity

DESCRIPTION

Benazepril hydrochloride is a white to off-white crystalline powder, soluble (>100 mg/mL) in water, in ethanol, and in methanol. Its chemical name is 3-[[1-(ethoxy-carbonyl)-3-phenyl-(1S)-propyl]amino]-2,3,4,5-tetrahydro-2-oxo-1H-1-(3S)-benzazepine-1-acetic acid monohydrochloride; its structural formula is

Its empirical formula is C24H28N2O5•HCl, and its molecular weight is 460.96.

Benazeprilat, the active metabolite of benazepril, is a non-sulfhydryl angiotensin-converting enzyme inhibitor. Benazepril is converted to benazeprilat by hepatic cleavage of the ester group.

Lotensin is supplied as tablets containing 5 mg, 10 mg, 20 mg, and 40 mg of benazepril hydrochloride for oral administration. The inactive ingredients are colloidal silicon dioxide, crospovidone, hydrogenated castor oil (5-mg, 10-mg, and 20-mg tablets), hypromellose, iron oxides, lactose, magnesium stearate (40-mg tablets), microcrystalline cellulose, polysorbate 80, propylene glycol (5-mg and 40-mg tablets), starch, talc, and titanium dioxide.

CLINICAL PHARMACOLOGY

Mechanism of Action

Benazepril and benazeprilat inhibit angiotensin-converting enzyme (ACE) in human subjects and animals. ACE is a peptidyl dipeptidase that catalyzes the conversion of angiotensin I to the vasoconstrictor substance, angiotensin II. Angiotensin II also stimulates aldosterone secretion by the adrenal cortex.

Inhibition of ACE results in decreased plasma angiotensin II, which leads to decreased vasopressor activity and to decreased aldosterone secretion. The latter decrease may result in a small increase of serum potassium. Hypertensive patients treated with Lotensin alone for up to 52 weeks had elevations of serum potassium of up to 0.2 mEq/L. Similar patients treated with Lotensin and hydrochlorothiazide for up to 24 weeks had no consistent changes in their serum potassium (see PRECAUTIONS).

Removal of angiotensin II negative feedback on renin secretion leads to increased plasma renin activity. In animal studies, benazepril had no inhibitory effect on the vasopressor response to angiotensin II and did not interfere with the hemodynamic effects of the autonomic neurotransmitters acetylcholine, epinephrine, and norepinephrine.

ACE is identical to kininase, an enzyme that degrades bradykinin. Whether increased levels of bradykinin, a potent vasodepressor peptide, play a role in the therapeutic effects of Lotensin remains to be elucidated.

While the mechanism through which benazepril lowers blood pressure is believed to be primarily suppression of the renin-angiotensin-aldosterone system, benazepril has an antihypertensive effect even in patients with low-renin hypertension (see INDICATIONS AND USAGE).

Pharmacokinetics and Metabolism

Following oral administration of Lotensin, peak plasma concentrations of benazepril are reached within 0.5-1.0 hours. The extent of absorption is at least 37% as determined by urinary recovery and is not significantly influenced by the presence of food in the GI tract.

Cleavage of the ester group (primarily in the liver) converts benazepril to its active metabolite, benazeprilat. Peak plasma concentrations of benazeprilat are reached 1-2 hours after drug intake in the fasting state and 2-4 hours after drug intake in the nonfasting state. The serum protein binding of benazepril is about 96.7% and that of benazeprilat about 95.3%, as measured by equilibrium dialysis; on the basis of in vitro studies, the degree of protein binding should be unaffected by age, hepatic dysfunction, or concentration (over the concentration range of 0.24-23.6 µmol/L).

Benazepril is almost completely metabolized to benazeprilat, which has much greater ACE inhibitory activity than benazepril, and to the glucuronide conjugates of benazepril and benazeprilat. Only trace amounts of an administered dose of Lotensin can be recovered in the urine as unchanged benazepril, while about 20% of the dose is excreted as benazeprilat, 4% as benazepril glucuronide, and 8% as benazeprilat glucuronide.

The kinetics of benazepril are approximately dose-proportional within the dosage range of 10-80 mg.

In adults, the effective half-life of accumulation of benazeprilat following multiple dosing of benazepril hydrochloride is 10-11 hours. Thus, steady-state concentrations of benazeprilat should be reached after 2 or 3 doses of benazepril hydrochloride given once daily.

The kinetics did not change, and there was no significant accumulation during chronic administration (28 days) of once-daily doses between 5 mg and 20 mg. Accumulation ratios based on AUC and urinary recovery of benazeprilat were 1.19 and 1.27, respectively.

Benazepril and benazeprilat are cleared predominantly by renal excretion in healthy subjects with normal renal function. Nonrenal (i.e., biliary) excretion accounts for approximately 11%-12% of benazeprilat excretion in healthy subjects. In patients with renal failure, biliary clearance may compensate to an extent for deficient renal clearance.

In patients with renal insufficiency, the disposition of benazepril and benazeprilat in patients with mild-to-moderate renal insufficiency (creatinine clearance >30 mL/min) is similar to that in patients with normal renal function. In patients with creatinine clearance ≤30 mL/min, peak benazeprilat levels and the initial (alpha phase) half-life increase, and time to steady state may be delayed (see DOSAGE AND ADMINISTRATION).

When dialysis was started 2 hours after ingestion of 10 mg of benazepril, approximately 6% of benazeprilat was removed in 4 hours of dialysis. The parent compound, benazepril, was not detected in the dialysate.

In patients with hepatic insufficiency (due to cirrhosis), the pharmacokinetics of benazeprilat are essentially unaltered. The pharmacokinetics of benazepril and benazeprilat do not appear to be influenced by age.

In pediatric patients, (N=45) hypertensive, age 6 to 16 years, given multiple daily doses of Lotensin (0.1 to 0.5 mg/kg), the clearance of benazeprilat for children 6 to 12 years old was 0.35 L/hr/kg, more than twice that of healthy adults receiving a single dose of 10 mg (0.13 L/hr/kg). In adolescents, it was 0.17 L/hr/kg, 27% higher than that of healthy adults. The terminal elimination half-life of benazeprilat in pediatric patients was around 5 hours, one-third that observed in adults.

Pharmacodynamics

Single and multiple doses of 10 mg or more of Lotensin cause inhibition of plasma ACE activity by at least 80%-90% for at least 24 hours after dosing. Pressor responses to exogenous angiotensin I were inhibited by 60%-90% (up to 4 hours post-dose) at the 10-mg dose.

Hypertension

Adult

Administration of Lotensin to patients with mild-to-moderate hypertension results in a reduction of both supine and standing blood pressure to about the same extent with no compensatory tachycardia. Symptomatic postural hypotension is infrequent, although it can occur in patients who are salt- and/or volume-depleted (see WARNINGS).

In single-dose studies, Lotensin lowered blood pressure within 1 hour, with peak reductions achieved 2-4 hours after dosing. The antihypertensive effect of a single dose persisted for 24 hours. In multiple-dose studies, once-daily doses of 20-80 mg decreased seated pressure (systolic/diastolic) 24 hours after dosing by about 6-12/4-7 mmHg. The trough values represent reductions of about 50% of that seen at peak.

Four dose-response studies using once-daily dosing were conducted in 470 mild-to-moderate hypertensive patients not using diuretics. The minimal effective once-daily dose of Lotensin was 10 mg; but further falls in blood pressure, especially at morning trough, were seen with higher doses in the studied dosing range (10-80 mg). In studies comparing the same daily dose of Lotensin given as a single morning dose or as a twice-daily dose, blood pressure reductions at the time of morning trough blood levels were greater with the divided regimen.

During chronic therapy, the maximum reduction in blood pressure with any dose is generally achieved after 1-2 weeks. The antihypertensive effects of Lotensin have continued during therapy for at least two years. Abrupt withdrawal of Lotensin has not been associated with a rapid increase in blood pressure.

In patients with mild-to-moderate hypertension, Lotensin 10-20 mg was similar in effectiveness to captopril, hydrochlorothiazide, nifedipine SR, and propranolol.

The antihypertensive effects of Lotensin were not appreciably different in patients receiving high- or low-sodium diets.

In hemodynamic studies in dogs, blood pressure reduction was accompanied by a reduction in peripheral arterial resistance, with an increase in cardiac output and renal blood flow and little or no change in heart rate. In normal human volunteers, single doses of benazepril caused an increase in renal blood flow but had no effect on glomerular filtration rate.

Use of Lotensin in combination with thiazide diuretics gives a blood-pressure-lowering effect greater than that seen with either agent alone. By blocking the renin-angiotensin-aldosterone axis, administration of Lotensin tends to reduce the potassium loss associated with the diuretic.

Pediatric

In a clinical study of 107 pediatric patients, 7 to 16 years of age, with either systolic or diastolic pressure above the 95th percentile, patients were given 0.1 or 0.2 mg/kg then titrated up to 0.3 or 0.6 mg/kg with a maximum dose of 40 mg once daily. After four weeks of treatment, the 85 patients whose blood pressure was reduced on therapy were then randomized to either placebo or benazepril and were followed up for an additional two weeks. At the end of two weeks, blood pressure (both systolic and diastolic) in children withdrawn to placebo rose by 4 to 6 mmHg more than in children on benazepril. No dose-response was observed for the three doses.

INDICATIONS AND USAGE

Lotensin is indicated for the treatment of hypertension. It may be used alone or in combination with thiazide diuretics.

In using Lotensin, consideration should be given to the fact that another angiotensin-converting enzyme inhibitor, captopril, has caused agranulocytosis, particularly in patients with renal impairment or collagen-vascular disease. Available data are insufficient to show that Lotensin does not have a similar risk (see WARNINGS).

Black patients receiving ACE inhibitors have been reported to have a higher incidence of angioedema compared to nonblacks. It should also be noted that in controlled clinical trials ACE inhibitors have an effect on blood pressure that is less in black patients than in nonblacks.

CONTRAINDICATIONS

Lotensin is contraindicated in patients who are hypersensitive to this product or to any other ACE inhibitor.

Lotensin is also contraindicated in patients with a history of angioedema with or without previous ACE inhibitor treatment.

WARNINGS

Anaphylactoid and Possibly Related Reactions

Presumably because angiotensin-converting enzyme inhibitors affect the metabolism of eicosanoids and polypeptides, including endogenous bradykinin, patients receiving ACE inhibitors (including Lotensin) may be subject to a variety of adverse reactions, some of them serious.

Head and Neck Angioedema: Angioedema of the face, extremities, lips, tongue, glottis, and larynx has been reported in patients treated with angiotensin-converting enzyme inhibitors. In U.S. clinical trials, symptoms consistent with angioedema were seen in none of the subjects who received placebo and in about 0.5% of the subjects who received Lotensin. Angioedema associated with laryngeal edema can be fatal. If laryngeal stridor or angioedema of the face, tongue, or glottis occurs, treatment with Lotensin should be discontinued and appropriate therapy instituted immediately. Where there is involvement of the tongue, glottis, or larynx, likely to cause airway obstruction, appropriate therapy, e.g., subcutaneous epinephrine injection 1:1000 (0.3 mL to 0.5 mL) should be promptly administered (see ADVERSE REACTIONS).

Intestinal Angioedema: Intestinal angioedema has been reported in patients treated with ACE inhibitors. These patients presented with abdominal pain (with or without nausea or vomiting); in some cases there was no prior history of facial angioedema and C-1 esterase levels were normal. The angioedema was diagnosed by procedures including abdominal CT scan or ultrasound, or at surgery, and symptoms resolved after stopping the ACE inhibitor. Intestinal angioedema should be included in the differential diagnosis of patients on ACE inhibitors presenting with abdominal pain.

Anaphylactoid Reactions During Desensitization: Two patients undergoing desensitizing treatment with hymenoptera venom while receiving ACE inhibitors sustained life-threatening anaphylactoid reactions. In the same patients, these reactions were avoided when ACE inhibitors were temporarily withheld, but they reappeared upon inadvertent rechallenge.

Anaphylactoid Reactions During Membrane Exposure: Anaphylactoid reactions have been reported in patients dialyzed with high-flux membranes and treated concomitantly with an ACE inhibitor. Anaphylactoid reactions have also been reported in patients undergoing low-density lipoprotein apheresis with dextran sulfate absorption (a procedure dependent upon devices not approved in the United States).

Hypotension

Lotensin can cause symptomatic hypotension. Like other ACE inhibitors, benazepril has been only rarely associated with hypotension in uncomplicated hypertensive patients. Symptomatic hypotension is most likely to occur in patients who have been volume-and/or salt-depleted as a result of prolonged diuretic therapy, dietary salt restriction, dialysis, diarrhea, or vomiting. Volume-and/or salt-depletion should be corrected before initiating therapy with Lotensin.

In patients with congestive heart failure, with or without associated renal insufficiency, ACE inhibitor therapy may cause excessive hypotension, which may be associated with oliguria or azotemia and, rarely, with acute renal failure and death. In such patients, Lotensin therapy should be started under close medical supervision; they should be followed closely for the first 2 weeks of treatment and whenever the dose of benazepril or diuretic is increased.

If hypotension occurs, the patient should be placed in a supine position, and, if necessary, treated with intravenous infusion of physiological saline. Lotensin treatment usually can be continued following restoration of blood pressure and volume.

Neutropenia/Agranulocytosis

Another angiotensin-converting enzyme inhibitor, captopril, has been shown to cause agranulocytosis and bone marrow depression, rarely in uncomplicated patients, but more frequently in patients with renal impairment, especially if they also have a collagen-vascular disease such as systemic lupus erythematosus or scleroderma. Available data from clinical trials of benazepril are insufficient to show that benazepril does not cause agranulocytosis at similar rates. Monitoring of white blood cell counts should be considered in patients with collagen-vascular disease, especially if the disease is associated with impaired renal function.

Fetal toxicity

Pregnancy category D

Use of drugs that act on the renin-angiotensin system during the second and third trimesters of pregnancy reduces fetal renal function and increases fetal and neonatal morbidity and death. Resulting oligohydramnios can be associated with fetal lung hypoplasia and skeletal deformations. Potential neonatal adverse effects include skull hypoplasia, anuria, hypotension, renal failure, and death. When pregnancy is detected, discontinue Lotensin as soon as possible. These adverse outcomes are usually associated with use of these drugs in the second and third trimester of pregnancy. Most epidemiologic studies examining fetal abnormalities after exposure to antihypertensive use in the first trimester have not distinguished drugs affecting the renin-angiotensin system from other antihypertensive agents. Appropriate management of maternal hypertension during pregnancy is important to optimize outcomes for both mother and fetus.

In the unusual case that there is no appropriate alternative to therapy with drugs affecting the renin-angiotensin system for a particular patient, apprise the mother of the potential risk to the fetus. Perform serial ultrasound examinations to assess the intra-amniotic environment. If oligohydramnios is observed, discontinue Lotensin, unless it is considered lifesaving for the mother. Fetal testing may be appropriate, based on the week of pregnancy. Patients and physicians should be aware, however, that oligohydramnios may not appear until after the fetus has sustained irreversible injury. Closely observe infants with histories of in utero exposure to Lotensin for hypotension, oliguria, and hyperkalemia. [see Precautions, Pediatric Use]

No teratogenic effects of Lotensin were seen in studies of pregnant rats, mice, and rabbits. On a mg/m2 basis, the doses used in these studies were 60 times (in rats), 9 times (in mice), and more than 0.8 times (in rabbits) the maximum recommended human dose (assuming a 50-kg woman). On a mg/kg basis these multiples are 300 times (in rats), 90 times (in mice), and more than 3 times (in rabbits) the maximum recommended human dose.

Hepatic Failure

Rarely, ACE inhibitors have been associated with a syndrome that starts with cholestatic jaundice and progresses to fulminant hepatic necrosis and (sometimes) death. The mechanism of this syndrome is not understood. Patients receiving ACE inhibitors who develop jaundice or marked elevations of hepatic enzymes should discontinue the ACE inhibitor and receive appropriate medical follow-up.

PRECAUTIONS

General

Impaired Renal Function: As a consequence of inhibiting the renin-angiotensin-aldosterone system, changes in renal function may be anticipated in susceptible individuals. In patients with severe congestive heart failure whose renal function may depend on the activity of the renin-angiotensin-aldosterone system, treatment with angiotensin-converting enzyme inhibitors, including Lotensin, may be associated with oliguria and/or progressive azotemia and (rarely) with acute renal failure and/or death. In a small study of hypertensive patients with renal artery stenosis in a solitary kidney or bilateral renal artery stenosis, treatment with Lotensin was associated with increases in blood urea nitrogen and serum creatinine; these increases were reversible upon discontinuation of Lotensin or diuretic therapy, or both. When such patients are treated with ACE inhibitors, renal function should be monitored during the first few weeks of therapy. Some hypertensive patients with no apparent preexisting renal vascular disease have developed increases in blood urea nitrogen and serum creatinine, usually minor and transient, especially when Lotensin has been given concomitantly with a diuretic. This is more likely to occur in patients with preexisting renal impairment. Dosage reduction of Lotensin and/or discontinuation of the diuretic may be required. Evaluation of the hypertensive patient should always include assessment of renal function (see DOSAGE AND ADMINISTRATION).

Hyperkalemia: In clinical trials, hyperkalemia (serum potassium at least 0.5 mEq/L greater than the upper limit of normal) occurred in approximately 1% of hypertensive patients receiving Lotensin. In most cases, these were isolated values which resolved despite continued therapy. Risk factors for the development of hyperkalemia include renal insufficiency, diabetes mellitus, and the concomitant use of potassium-sparing diuretics, potassium supplements, and/or potassium-containing salt substitutes, which should be used cautiously, if at all, with Lotensin (see Drug Interactions).

Cough: Presumably due to the inhibition of the degradation of endogenous bradykinin, persistent nonproductive cough has been reported with all ACE inhibitors, always resolving after discontinuation of therapy. ACE inhibitor-induced cough should be considered in the differential diagnosis of cough.

Impaired Liver Function: In patients with hepatic dysfunction due to cirrhosis, levels of benazeprilat are essentially unaltered (see WARNINGS, Hepatic Failure).

Surgery/Anesthesia: In patients undergoing surgery or during anesthesia with agents that produce hypotension, benazepril will block the angiotensin II formation that could otherwise occur secondary to compensatory renin release. Hypotension that occurs as a result of this mechanism can be corrected by volume expansion.

Information for Patients

Pregnancy: Female patients of childbearing age should be told about the consequences of exposure to Lotensin during pregnancy. Discuss treatment options with women planning to become pregnant. Patients should be asked to report pregnancies to their physicians as soon as possible.

Angioedema: Angioedema, including laryngeal edema, can occur at any time with treatment with ACE inhibitors. Patients should be so advised and told to report immediately any signs or symptoms suggesting angioedema (swelling of face, eyes, lips, or tongue, or difficulty in breathing) and to take no more drug until they have consulted with the prescribing physician.

Symptomatic Hypotension: Patients should be cautioned that lightheadedness can occur, especially during the first days of therapy, and it should be reported to the prescribing physician. Patients should be told that if syncope occurs, Lotensin should be discontinued until the prescribing physician has been consulted.

All patients should be cautioned that inadequate fluid intake or excessive perspiration, diarrhea, or vomiting can lead to an excessive fall in blood pressure, with the same consequences of lightheadedness and possible syncope.

Hyperkalemia: Patients should be told not to use potassium supplements or salt substitutes containing potassium without consulting the prescribing physician.

Neutropenia: Patients should be told to promptly report any indication of infection (e.g., sore throat, fever), which could be a sign of neutropenia.

Drug Interactions

Diuretics: Patients on diuretics, especially those in whom diuretic therapy was recently instituted, may occasionally experience an excessive reduction of blood pressure after initiation of therapy with Lotensin. The possibility of hypotensive effects with Lotensin can be minimized by either discontinuing the diuretic or increasing the salt intake prior to initiation of treatment with Lotensin. If this is not possible, the starting dose should be reduced (see DOSAGE AND ADMINISTRATION).

Potassium Supplements and Potassium-Sparing Diuretics: Lotensin can attenuate potassium loss caused by thiazide diuretics. Potassium-sparing diuretics (spironolactone, amiloride, triamterene, and others) or potassium supplements can increase the risk of hyperkalemia. Therefore, if concomitant use of such agents is indicated, they should be given with caution, and the patient’s serum potassium should be monitored frequently.

Oral Anticoagulants: Interaction studies with warfarin and acenocoumarol failed to identify any clinically important effects on the serum concentrations or clinical effects of these anticoagulants.

Lithium: Increased serum lithium levels and symptoms of lithium toxicity have been reported in patients receiving ACE inhibitors (including benazepril) during therapy with lithium. These drugs should be coadministered with caution, and frequent monitoring of serum lithium levels is recommended. If a diuretic is also used, the risk of lithium toxicity may be increased.

Gold: Nitritoid reactions (symptoms include facial flushing, nausea, vomiting and hypotension) have been reported rarely in patients on therapy with injectable gold (sodium aurothiomalate) and concomitant ACE inhibitor therapy.

Anti-diabetics: In rare cases, diabetic patients receiving an ACE inhibitor (including benazepril) concomitantly with insulin or oral anti-diabetics may develop hypoglycemia. Such patients should therefore be advised about the possibility of hypoglycemic reactions and should be monitored accordingly.

Non-Steroidal Anti-Inflammatory Agents including Selective Cyclooxygenase-2 Inhibitors (COX-2 Inhibitors): In patients who are elderly, volume-depleted (including those on diuretic therapy), or with compromised renal function, co-administration of NSAIDs, including selective COX-2 inhibitors, with ACE inhibitors, including benazepril, may result in deterioration of renal function, including possible acute renal failure. These effects are usually reversible. Monitor renal function periodically in patients receiving benazepril and NSAID therapy.

The antihypertensive effect of ACE inhibitors, including benazepril, may be attenuated by NSAIDs.

Other: No clinically important pharmacokinetic interactions occurred when Lotensin was administered concomitantly with hydrochlorothiazide, chlorthalidone, furosemide, digoxin, propranolol, atenolol, or cimetidine.

Lotensin has been used concomitantly with beta-adrenergic-blocking agents, calcium-channel-blocking agents, diuretics, digoxin, and hydralazine, without evidence of clinically important adverse interactions. Benazepril, like other ACE inhibitors, has had less than additive effects with beta-adrenergic blockers, presumably because both drugs lower blood pressure by inhibiting parts of the renin-angiotensin system.

Carcinogenesis, Mutagenesis, Impairment of Fertility

No evidence of carcinogenicity was found when benazepril was administered to rats and mice for up to two years at doses of up to 150 mg/kg/day. When compared on the basis of body weights, this dose is 110 times the maximum recommended human dose. When compared on the basis of body surface areas, this dose is 18 and 9 times (rats and mice, respectively) the maximum recommended human dose (calculations assume a patient weight of 60 kg). No mutagenic activity was detected in the Ames test in bacteria (with or without metabolic activation), in an in vitro test for forward mutations in cultured mammalian cells, or in a nucleus anomaly test. In doses of 50-500 mg/kg/day (6-60 times the maximum recommended human dose based on mg/m^2 comparison and 37-375 times the maximum recommended human dose based on a mg/kg comparison), Lotensin had no adverse effect on the reproductive performance of male and female rats.

Nursing Mothers

Minimal amounts of unchanged benazepril and of benazeprilat are excreted into the breast milk of lactating women treated with benazepril. A newborn child ingesting entirely breast milk would receive less than 0.1% of the mg/kg maternal dose of benazepril and benazeprilat.

Geriatric Use

Of the total number of patients who received benazepril in U.S. clinical studies of Lotensin, 18% were 65 or older while 2% were 75 or older. No overall differences in effectiveness or safety were observed between these patients and younger patients, and other reported clinical experience has not identified differences in responses between the elderly and younger patients, but greater sensitivity of some older individuals cannot be ruled out.

Benazepril and benazeprilat are substantially excreted by the kidney. Because elderly patients are more likely to have decreased renal function, care should be taken in dose selection, and it may be useful to monitor renal function.

Pediatric Use

Neonates with a history of in utero exposure to Lotensin:

If oliguria or hypotension occurs, direct attention toward support of blood pressure and renal perfusion. Exchange transfusions or dialysis may be required as a means of reversing hypotension and/or substituting for disordered renal function. Benazepril, which crosses the placenta, can theoretically be removed from the neonatal circulation by these means; there are occasional reports of benefit from these maneuvers with another ACE inhibitor, but experience is limited.

The antihypertensive effects of Lotensin have been evaluated in a double-blind study in pediatric patients 7 to 16 years of age (see CLINICAL PHARMACOLOGY: Pharmacodynamics, Hypertension). The pharmacokinetics of Lotensin have been evaluated in pediatric patients 6 to 16 years of age (see CLINICAL PHARMACOLOGY: Pharmacokinetics and Metabolism). Lotensin was generally well tolerated and adverse effects were similar to those described in adults. (See ADVERSE REACTIONS: Pediatric Patients).

Treatment with Lotensin is not recommended in pediatric patients less than 6 years of age (see ADVERSE REACTIONS), and in children with glomerular filtration rate <30 mL/min as there are insufficient data available to support a dosing recommendation in these groups. (See CLINICAL PHARMACOLOGY: Pharmacokinetics and Metabolism, In Pediatric Patients and DOSAGE AND ADMINISTRATION.)

ADVERSE REACTIONS

Lotensin has been evaluated for safety in over 6000 patients with hypertension; over 700 of these patients were treated for at least one year. The overall incidence of reported adverse events was comparable in Lotensin and placebo patients.

The reported side effects were generally mild and transient, and there was no relation between side effects and age, duration of therapy, or total dosage within the range of 2 to 80 mg. Discontinuation of therapy because of a side effect was required in approximately 5% of U.S. patients treated with Lotensin and in 3% of patients treated with placebo.

The most common reasons for discontinuation were headache (0.6%) and cough (0.5%) (see PRECAUTIONS, Cough).

The side effects considered possibly or probably related to study drug that occurred in U.S. placebo-controlled trials in more than 1% of patients treated with Lotensin are shown below.

PATIENTS IN U.S. PLACEBO-CONTROLLED STUDIES
 | LOTENSIN (N=964) |  | PLACEBO (N=496)
 | N | % | N | %
Headache | 60 | 6.2 | 21 | 4.2
Dizziness | 35 | 3.6 | 12 | 2.4
Fatigue | 23 | 2.4 | 11 | 2.2
Somnolence | 15 | 1.6 | 2 | 0.4
Postural Dizziness | 14 | 1.5 | 1 | 0.2
Nausea | 13 | 1.3 | 5 | 1.0
Cough | 12 | 1.2 | 5 | 1.0

Other adverse experiences reported in controlled clinical trials (in less than 1% of benazepril patients), and rarer events seen in post-marketing experience, include the following (in some, a causal relationship to drug use is uncertain):

Cardiovascular: Symptomatic hypotension was seen in 0.3% of patients, postural hypotension in 0.4%, and syncope in 0.1%; these reactions led to discontinuation of therapy in 4 patients who had received benazepril monotherapy and in 9 patients who had received benazepril with hydrochlorothiazide (see PRECAUTIONS and WARNINGS). Other reports included angina pectoris, palpitations, and peripheral edema.

Renal: Of hypertensive patients with no apparent preexisting renal disease, about 2% have sustained increases in serum creatinine to at least 150% of their baseline values while receiving Lotensin, but most of these increases have disappeared despite continuing treatment. A much smaller fraction of these patients (less than 0.1%) developed simultaneous (usually transient) increases in blood urea nitrogen and serum creatinine.

Angioedema: Angioedema has been reported in patients receiving ACE inhibitors. During clinical trials in hypertensive patients with benazepril, 0.5% of patients experienced edema of the lips or face without other manifestations of angioedema. Angioedema associated with laryngeal edema and/or shock may be fatal. If angioedema of the face, extremities, lips, tongue, or glottis and/or larynx occurs, treatment with Lotensin should be discontinued and appropriate therapy instituted immediately (see WARNINGS).

Dermatologic: Stevens-Johnson syndrome, pemphigus, apparent hypersensitivity reactions (manifested by dermatitis, pruritus, or rash), photosensitivity, and flushing.

Gastrointestinal: Pancreatitis, constipation, gastritis, vomiting, and melena.

Hematologic: Thrombocytopenia and hemolytic anemia.

Neurologic and Psychiatric: Anxiety, decreased libido, hypertonia, insomnia, nervousness, and paresthesia.

Other: Asthma, bronchitis, dyspnea, sinusitis, urinary tract infection, frequent urination, infection, arthritis, impotence, alopecia, arthralgia, myalgia, asthenia, and sweating.

Another potentially important adverse experience, eosinophilic pneumonitis, has been attributed to other ACE inhibitors.

The following adverse events of unknown frequency have been reported during post-marketing use of benazepril: small bowel angioedema, anaphylactoid reactions, hyperkalemia, agranulocytosis, and neutropenia.

Pediatric Patients: The adverse experience profile for pediatric patients appears to be similar to that seen in adult patients. Infants below the age of 1 year should not be given ACE inhibitors due to concerns over possible effects on kidney development.

The long-term effects of benazepril on growth and development have not been studied.

Clinical Laboratory Test Findings

Creatinine and Blood Urea Nitrogen: Of hypertensive patients with no apparent preexisting renal disease, about 2% have sustained increases in serum creatinine to at least 150% of their baseline values while receiving Lotensin, but most of these increases have disappeared despite continuing treatment. A much smaller fraction of these patients (less than 0.1%) developed simultaneous (usually transient) increases in blood urea nitrogen and serum creatinine. None of these increases required discontinuation of treatment. Increases in these laboratory values are more likely to occur in patients with renal insufficiency or those pretreated with a diuretic and, based on experience with other ACE inhibitors, would be expected to be especially likely in patients with renal artery stenosis (see PRECAUTIONS, General).

Potassium: Since benazepril decreases aldosterone secretion, elevation of serum potassium can occur. Potassium supplements and potassium-sparing diuretics should be given with caution, and the patient’s serum potassium should be monitored frequently (see PRECAUTIONS).

Hemoglobin: Decreases in hemoglobin (a low value and a decrease of 5 g/dL) were rare, occurring in only 1 of 2,014 patients receiving Lotensin alone and in 1 of 1,357 patients receiving Lotensin plus a diuretic. No U.S. patients discontinued treatment because of decreases in hemoglobin.

Other (causal relationships unknown): Clinically important changes in standard laboratory tests were rarely associated with Lotensin administration. Elevations of uric acid, blood glucose, serum bilirubin, and liver enzymes (see WARNINGS) have been reported, as have scattered incidents of hyponatremia, electrocardiographic changes, leukopenia, eosinophilia, and proteinuria. In U.S. trials, less than 0.5% of patients discontinued treatment because of laboratory abnormalities.

OVERDOSAGE

Single oral doses of 3 g/kg benazepril were associated with significant lethality in mice. Rats, however, tolerated single oral doses of up to 6 g/kg. Reduced activity was seen at 1 g/kg in mice and at 5 g/kg in rats. Human overdoses of benazepril have not been reported, but the most common manifestation of human benazepril overdosage is likely to be hypotension.

Laboratory determinations of serum levels of benazepril and its metabolites are not widely available, and such determinations have, in any event, no established role in the management of benazepril overdose.

No data are available to suggest physiological maneuvers (e.g., maneuvers to change the pH of the urine) that might accelerate elimination of benazepril and its metabolites. Benazepril is only slightly dialyzable, but dialysis might be considered in overdosed patients with severely impaired renal function (see WARNINGS).

Angiotensin II could presumably serve as a specific antagonist-antidote in the setting of benazepril overdose, but angiotensin II is essentially unavailable outside of scattered research facilities. Because the hypotensive effect of benazepril is achieved through vasodilation and effective hypovolemia, it is reasonable to treat benazepril overdose by infusion of normal saline solution.

DOSAGE AND ADMINISTRATION

Hypertension

Adults

The recommended initial dose for patients not receiving a diuretic is 10 mg once a day. The usual maintenance dosage range is 20-40 mg per day administered as a single dose or in two equally divided doses. A dose of 80 mg gives an increased response, but experience with this dose is limited. The divided regimen was more effective in controlling trough (pre-dosing) blood pressure than the same dose given as a once-daily regimen. Dosage adjustment should be based on measurement of peak (2-6 hours after dosing) and trough responses. If a once-daily regimen does not give adequate trough response, an increase in dosage or divided administration should be considered. If blood pressure is not controlled with Lotensin alone, a diuretic can be added.

Total daily doses above 80 mg have not been evaluated.

Concomitant administration of Lotensin with potassium supplements, potassium salt substitutes, or potassium-sparing diuretics can lead to increases of serum potassium (see PRECAUTIONS).

In patients who are currently being treated with a diuretic, symptomatic hypotension occasionally can occur following the initial dose of Lotensin. To reduce the likelihood of hypotension, the diuretic should, if possible, be discontinued two to three days prior to beginning therapy with Lotensin (see WARNINGS). Then, if blood pressure is not controlled with Lotensin alone, diuretic therapy should be resumed.

If the diuretic cannot be discontinued, an initial dose of 5 mg Lotensin should be used to avoid excessive hypotension.

Pediatrics

In children, doses of Lotensin between 0.1 and 0.6 mg/kg once daily have been studied, and doses greater than 0.1 mg/kg were shown to reduce blood pressure (see Pharmacodynamics). Based on this, the recommended starting dose of Lotensin is 0.2 mg/kg once per day as monotherapy. Doses above 0.6 mg/kg (or in excess of 40 mg daily) have not been studied in pediatric patients.

For pediatric patients who cannot swallow tablets, or for whom the calculated dosage (mg/kg) does not correspond to the available tablet strengths for Lotensin, follow the suspension preparation instructions below to administer benazepril HCl as a suspension.

Treatment with Lotensin is not advised for children below the age of 6 years (see PRECAUTIONS, Pediatric Use) and in pediatric patients with glomerular filtration rate <30 mL, as there are insufficient data available to support a dosing recommendation in these groups.

For Hypertensive Patients with Renal Impairment

For patients with a creatinine clearance <30 mL/min/1.73 m^2 (serum creatinine >3 mg/dL), the recommended initial dose is 5 mg Lotensin once daily. Dosage may be titrated upward until blood pressure is controlled or to a maximum total daily dose of 40 mg (see WARNINGS).

Preparation of Suspension (for 150 mL of a 2 mg/mL suspension)

Add 75 mL of Ora-Plus®* oral suspending vehicle to an amber polyethylene terephthalate (PET) bottle containing fifteen Lotensin 20 mg tablets, and shake for at least 2 minutes. Allow the suspension to stand for a minimum of 1 hour. After the standing time, shake the suspension for a minimum of 1 additional minute. Add 75 mL of Ora-Sweet®* oral syrup vehicle to the bottle and shake the suspension to disperse the ingredients. The suspension should be refrigerated at 2-8°C (36-46°F) and can be stored for up to 30 days in the PET bottle with a child-resistant screw-cap closure. Shake the suspension before each use.

*Ora-Plus® and Ora-Sweet® are registered trademarks of Paddock Laboratories, Inc. Ora-Plus® contains carrageenan, citric acid, methylparaben, microcrystalline cellulose, carboxymethylcellulose sodium, potassium sorbate, simethicone, sodium phosphate monobasic, xanthan gum, and water. Ora-Sweet® contains citric acid, berry citrus flavorant, glycerin, methylparaben, potassium sorbate, sodium phosphate monobasic, sorbitol, sucrose, and water.

HOW SUPPLIED

Lotensin is available in tablets of 5 mg, 10 mg, 20 mg, and 40 mg, packaged with a desiccant in bottles of 100 tablets.

Each tablet is imprinted with LOTENSIN on one side and the tablet strength (“5,” “10,” “20,” or “40”) on the other.

The National Drug Codes for the various packages are

Dosage | Color | Package Size | NDC Number
5 mg | light yellow | Bottles of 30 | NDC 54868-3690-1
10 mg | dark yellow | Bottles of 10 | NDC 54868-2350-4
 |  | Bottles of 30 | NDC 54868-2350-3
 |  | Bottles of 60 | NDC 54868-2350-1
 |  | Bottles of 100 | NDC 54868-2350-2
20 mg | pink | Bottles of 10 | NDC 54868-2351-2
 |  | Bottles of 30 | NDC 54868-2351-0
 |  | Bottles of 100 | NDC 54868-2351-3
40 mg | dark rose | Bottles of 10 | NDC 54868-2352-1
 |  | Bottles of 30 | NDC 54868-2352-0

Storage: Do not store above 30°C (86°F). Protect from moisture.

Dispense in tight container (USP).

Manufactured by:
Novartis Pharmaceuticals Corporation
Suffern, New York 10901

Distributed by:
Novartis Pharmaceuticals Corporation
East Hanover, New Jersey 07936

© Novartis

T2012-45

January 2012

Relabeling and Repackaging by:
Physicians Total Care, Inc.
Tulsa, Oklahoma 74146

PRINCIPAL DISPLAY PANEL

Package Label – 5 mg Tablets

Rx Only

Lotensin® benazepril HCI

5 mg

PRINCIPAL DISPLAY PANEL

Package Label – 10 mg Tablets

Rx Only

Lotensin® benazepril HCI

10 mg

PRINCIPAL DISPLAY PANEL

Package Label – 20 mg Tablets

Rx Only

Lotensin® benazepril HCI

20 mg

PRINCIPAL DISPLAY PANEL

Package Label – 40 mg Tablets

Rx Only

Lotensin® benazepril HCI

40 mg